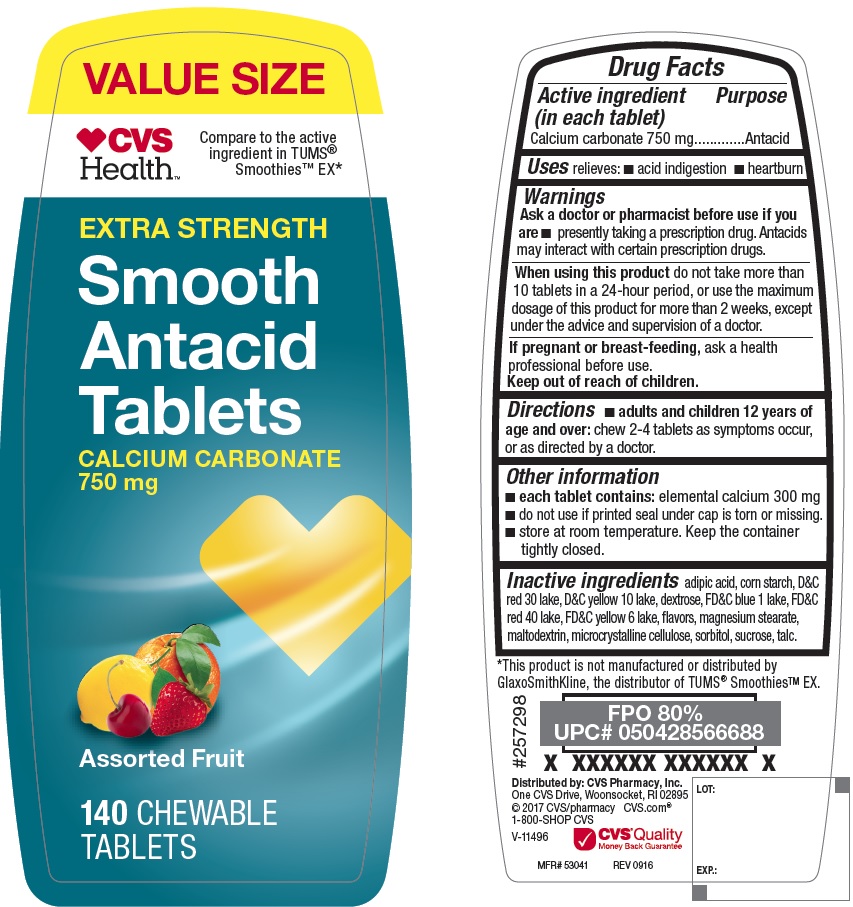 DRUG LABEL: Extra Strength Smooth Antacid Assorted Fruit
NDC: 69842-173 | Form: TABLET, CHEWABLE
Manufacturer: CVS
Category: otc | Type: HUMAN OTC DRUG LABEL
Date: 20170508

ACTIVE INGREDIENTS: CALCIUM CARBONATE 750 mg/1 1
INACTIVE INGREDIENTS: ADIPIC ACID; STARCH, CORN; D&C RED NO. 30; D&C YELLOW NO. 10; DEXTROSE; FD&C BLUE NO. 1; FD&C YELLOW NO. 6; MAGNESIUM STEARATE; MALTODEXTRIN; SUCROSE; TALC; FD&C RED NO. 40; MICROCRYSTALLINE CELLULOSE; SORBITOL

Extra Strength Smooth Antacid Tablets Assorted Fruit

Active ingredient (in each tablet)

Calcium carbonate 750 mg

Purpose

Antacid

Uses

relieves

- acid indigestion
- heartburn

Warnings

Ask a doctor or pharmacist before use if you are

- presently taking a prescription drug. Antacids may interact with certain prescription drugs.

When using this product

do not take more than 10 tablets in a 24-hour period, or use the maximum dosage of this product for more than 2 weeks, except under the advice and supervision of a doctor.

If pregnant or breast-feeding, ask a health professional before use.

Keep out of reach of children

Directions

- adults and children 12 years of age and over: chew 2-4 tablets as symptoms occur, or as directed by a doctor.

Other information

- each tablet contains: elemental calcium 300 mg
- do not use if printed seal under cap is torn or missing.
- store at room temperature. keep the container tightly closed.

Inactive ingredients

adipic acid, corn starch, D&C red 30 lake, D&C yellow 10 lake, dextrose, FD&C blue 1 lake, FD&C yellow 6 lake, FD&C red 40 lake, flavors, microcrystalline cellulose, magnesium stearate, maltodextrin, sorbitol, sucrose, talc

PACKAGE LABEL

*Compare to the active ingredient inTUMS® Smooth Extra Strength

Extra Strength Smooth Antacid Tablets

Calcium Carbonate 750 mg

Assorted Fruit Flavor

140 chewable Tablets